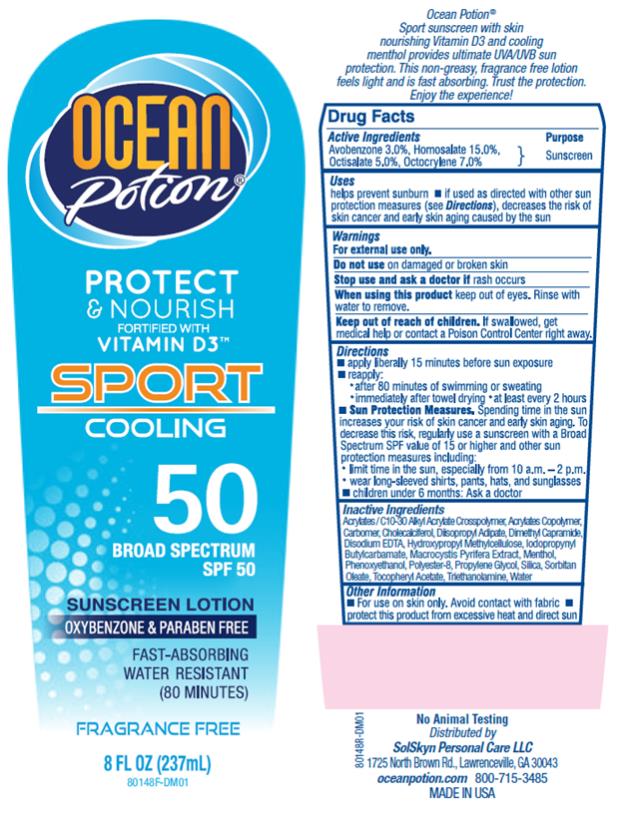 DRUG LABEL: OP spf50 and Sport Sunscreen
NDC: 70281-217 | Form: LOTION
Manufacturer: SolSkyn Personal Care LLC
Category: otc | Type: HUMAN OTC DRUG LABEL
Date: 20180215

ACTIVE INGREDIENTS: AVOBENZONE 3 g/100 g; HOMOSALATE 15 g/100 g; OCTISALATE 5 g/100 g; OCTOCRYLENE 7 g/100 g
INACTIVE INGREDIENTS: CARBOMER INTERPOLYMER TYPE A (55000 CPS); CARBOXYPOLYMETHYLENE; CHOLECALCIFEROL; DIISOPROPYL ADIPATE; DIMETHYL CAPRAMIDE; EDETATE DISODIUM ANHYDROUS; HYPROMELLOSE, UNSPECIFIED; IODOPROPYNYL BUTYLCARBAMATE; MACROCYSTIS PYRIFERA; MENTHOL; PHENOXYETHANOL; POLYESTER-8 (1400 MW, CYANODIPHENYLPROPENOYL CAPPED); PROPYLENE GLYCOL; SILICON DIOXIDE; SORBITAN MONOOLEATE; ALPHA-TOCOPHEROL ACETATE; TROLAMINE; WATER

OP-SPF50 8oz Sport Cooling Sunscreen Lotion

OP spf50+ Sport Sunscreen

Active ingredients:

Avobenzone 3.0%

Active ingredients:

Homosalate 15.0%

Active ingredients:

Octisalate 5.0%

Active ingredients:

Octocrylene 7.0%

Purpose

Sunscreen

Uses:

• Helps prevent sunburn.

• If used as directed with other sun protection measures (see Directions), decreases the risk of skin cancer and early skin aging caused by the sun.

Warnings:

• For external use only.

• Keep out of reach of children.

If swallowed, get medical help or contact a Poison Control Center right away.

Directions:

• Apply liberally 15 minutes before sun exposure.

• Re-apply:

• after 80 minutes of swimming or sweating

• immediately after towel drying

• at least every 2 hours

• Sun Protection Measures. Spending time in the sun increases your risk of skin cancer and early skin aging. To decrease this risk, regularly use a sunscreen with a Broad Spectrum SPF value of 15 or higher and other sun protection measures including:

• limit time in the sun, especially from 10 a.m.-2 p.m.

• wear long-sleeved shirts, pants, hats and sunglasses

• Children under 6 months: ask a doctor.

Inactive Ingredients:

Acrylates / C10-30 Alkyl Acrylate Crosspolymer, Acrylates Copolymer, Carbomer, Cholecalciferol, Diisopropyl Adipate, Dimethyl Capramide, Disodium EDTA, Hydroxypropyl Methylcellulose, Iodopropynyl Butylcarbamate, Macrocystis Pyrifera Extract, Menthol, Phenoxyethanol, Polyester-8, Propylene Glycol, Silica, Sorbitan Oleate, Tocopheryl Acetate, Triethanolamine, Water

Other Information:

• For use on skin only. Avoid contact with fabric.

• Protect this product from excessive heat and direct sun.

PRINCIPAL DISPLAY PANEL

Ocean Potion
Protect
& Nourish
Sport
cooling
SPF 50
8 fl oz (237 mL)